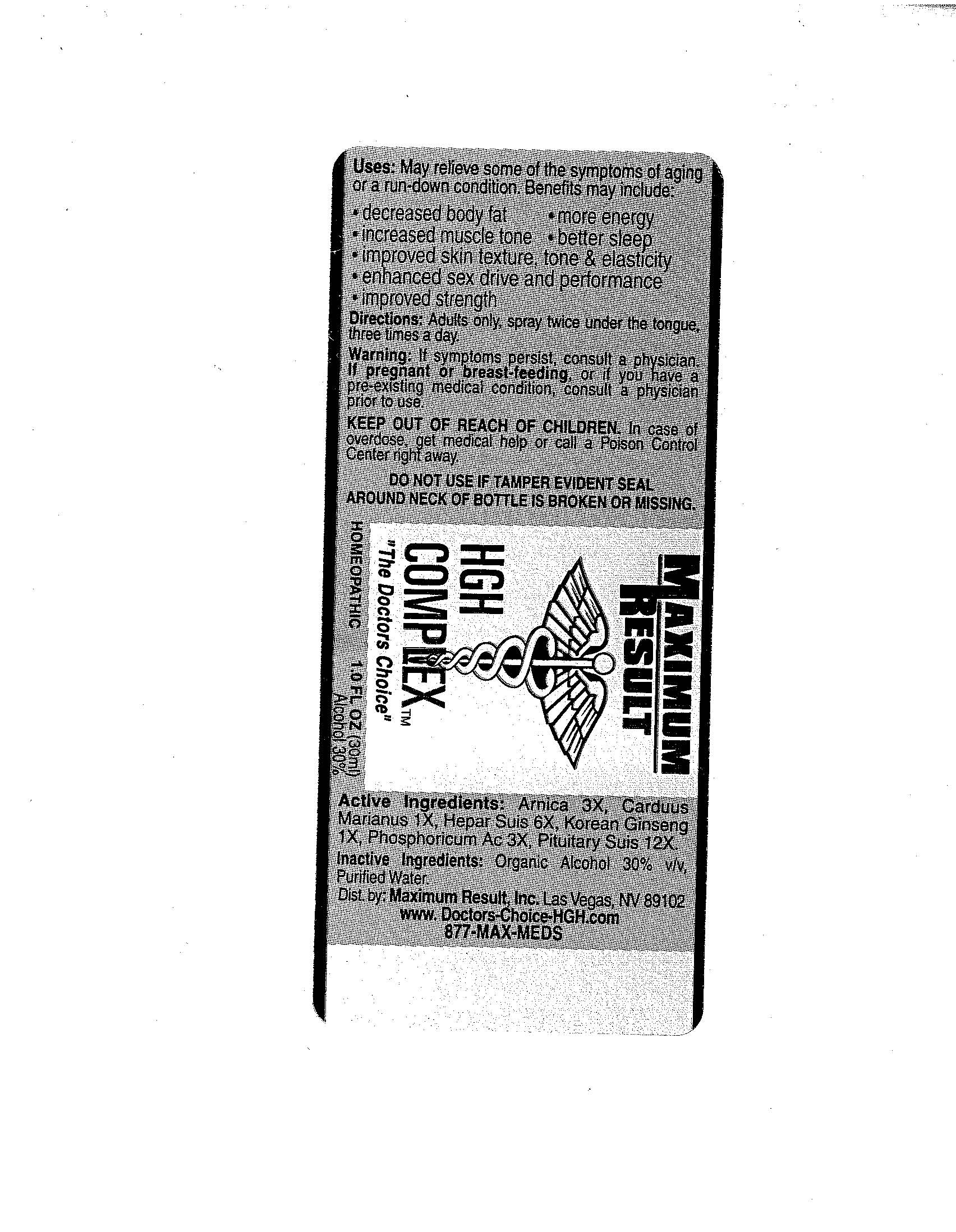 DRUG LABEL: HGH Complex
NDC: 50845-0016 | Form: SPRAY
Manufacturer: Liddell Laboratories, Inc.
Category: homeopathic | Type: HUMAN OTC DRUG LABEL
Date: 20100701

ACTIVE INGREDIENTS: ARNICA MONTANA 3 [hp_X]/1 mL; SILYBUM MARIANUM SEED 1 [hp_X]/1 mL; ASIAN GINSENG 1 [hp_X]/1 mL; PORK LIVER 3 [hp_X]/1 mL; PHOSPHORIC ACID 3 [hp_X]/1 mL; SUS SCROFA PITUITARY GLAND 12 [hp_X]/1 mL
INACTIVE INGREDIENTS: WATER; ALCOHOL

HGH Complex

PURPOSE

USES: May relieve some of the symptoms of aging or a run-down condition. Benefits may include: Decreased body fat, Increased muscle tone, Improved skin texture, tone and elasticity, Enhanced sex drive and performance, Improved strength, More energy, Better sleep.

DOSAGE AND ADMINISTRATION

DIRECTIONS: Adults only, spray twice under the tongue three times a day.

WARNINGS

WARNING: If symptoms persist, consult a physician. If pregnant or breast-feeding, or if you have a pre-existing medical condition, consult a physician prior to use.

KEEP OUT OF REACH OF CHILDREN. In case of overdose, get medical help or call a Poison Control Center right away.

DO NOT USE IF TAMPER EVIDENT SEAL AROUND NECK OF BOTTLE IS BROKEN OR MISSING.

ACTIVE INGREDIENT

ACTIVE INGREDIENTS: Arnica montana 3X, Carduus marianus 1X, Korean ginseng 1X, Liver (Porcine) 3X, Phosphoricum acidum 3X, Pituitary (Porcine) 12X.

INACTIVE INGREDIENTS: Organic alcohol 30%, Purified water

QUESTIONS

Dist. By:
Maximum Result, Inc.
Las Vegas, NV 89102
www.doctors-choice-HGH.com
877 MAX-MEDS

PACKAGE LABEL

MAXIMUM RESULT

HGH COMPLEX

The Doctors Choice

HOMEOPATHIC

1.0 FL OZ (30 ML)